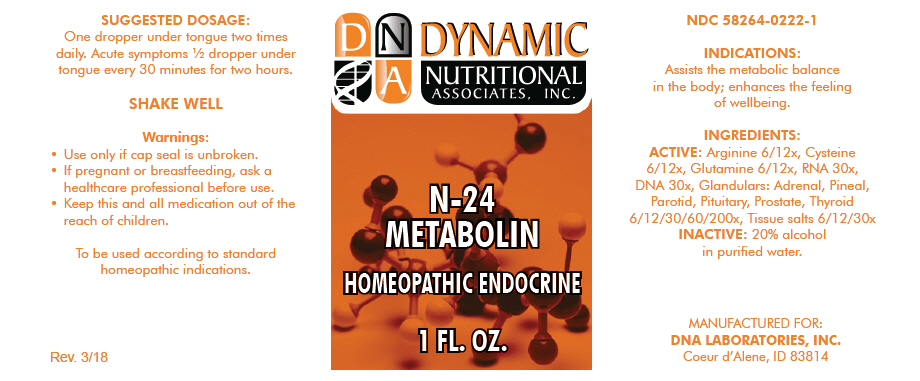 DRUG LABEL: N-24
NDC: 58264-0222 | Form: SOLUTION
Manufacturer: DNA Labs, Inc.
Category: homeopathic | Type: HUMAN OTC DRUG LABEL
Date: 20250109

ACTIVE INGREDIENTS: ARGININE 12 [hp_X]/1 mL; CYSTEINE 12 [hp_X]/1 mL; GLUTAMINE 12 [hp_X]/1 mL; SACCHAROMYCES CEREVISIAE RNA 30 [hp_X]/1 mL; HERRING SPERM DNA 30 [hp_X]/1 mL; BOS TAURUS ADRENAL GLAND 200 [hp_X]/1 mL; SUS SCROFA PINEAL GLAND 200 [hp_X]/1 mL; BOS TAURUS PAROTID GLAND 200 [hp_X]/1 mL; BOS TAURUS PITUITARY GLAND, POSTERIOR 200 [hp_X]/1 mL; BOS TAURUS PROSTATE GLAND 200 [hp_X]/1 mL; THYROID, UNSPECIFIED 200 [hp_X]/1 mL; CALCIUM FLUORIDE 30 [hp_X]/1 mL; TRIBASIC CALCIUM PHOSPHATE 30 [hp_X]/1 mL; CALCIUM SULFATE ANHYDROUS 30 [hp_X]/1 mL; FERROSOFERRIC PHOSPHATE 30 [hp_X]/1 mL; POTASSIUM CHLORIDE 30 [hp_X]/1 mL; DIBASIC POTASSIUM PHOSPHATE 30 [hp_X]/1 mL; POTASSIUM SULFATE 30 [hp_X]/1 mL; MAGNESIUM PHOSPHATE, DIBASIC TRIHYDRATE 30 [hp_X]/1 mL; SODIUM CHLORIDE 30 [hp_X]/1 mL; SODIUM PHOSPHATE, DIBASIC, HEPTAHYDRATE 30 [hp_X]/1 mL; SODIUM SULFATE 30 [hp_X]/1 mL; SILICON DIOXIDE 30 [hp_X]/1 mL
INACTIVE INGREDIENTS: ALCOHOL; WATER

N-24

NDC 58264-0222-1

INDICATIONS

PURPOSE

Assists the metabolic balance in the body; enhances the feeling of wellbeing.

INGREDIENTS

ACTIVE

Arginine 6/12x, Cysteine 6/12x, Glutamine 6/12x, RNA 30x, DNA 30x, Glandulars: Adrenal, Pineal, Parotid, Pituitary, Prostate, Thyroid 6/12/30/60/200x, Tissue salts 6/12/30x

INACTIVE

20% alcohol in purified water.

SUGGESTED DOSAGE

One dropper under tongue two times daily. Acute symptoms ½ dropper under tongue every 30 minutes for two hours.

STORAGE AND HANDLING

SHAKE WELL

Warnings

- Use only if cap seal is unbroken.

PREGNANCY OR BREAST FEEDING

- If pregnant or breastfeeding, ask a healthcare professional before use.

KEEP OUT OF REACH OF CHILDREN

- Keep this and all medication out of the reach of children.

To be used according to standard homeopathic indications.

PRINCIPAL DISPLAY PANEL - 1 FL. OZ. Bottle Label

DYNAMIC
NUTRITIONAL
ASSOCIATES, INC.

N-24
METABOLIN

HOMEOPATHIC ENDOCRINE

1 FL. OZ.